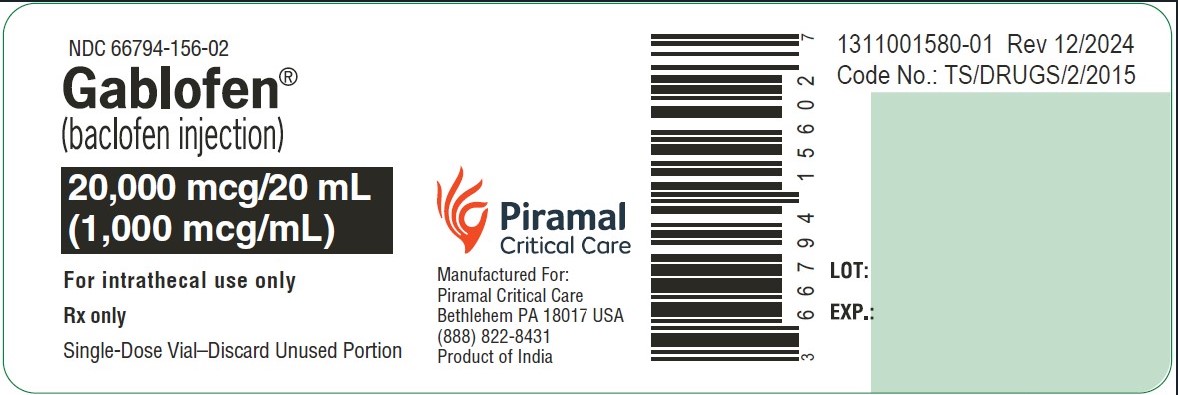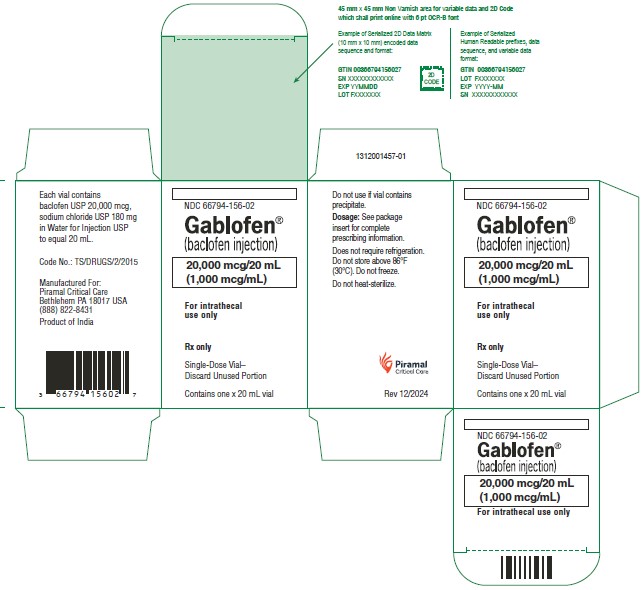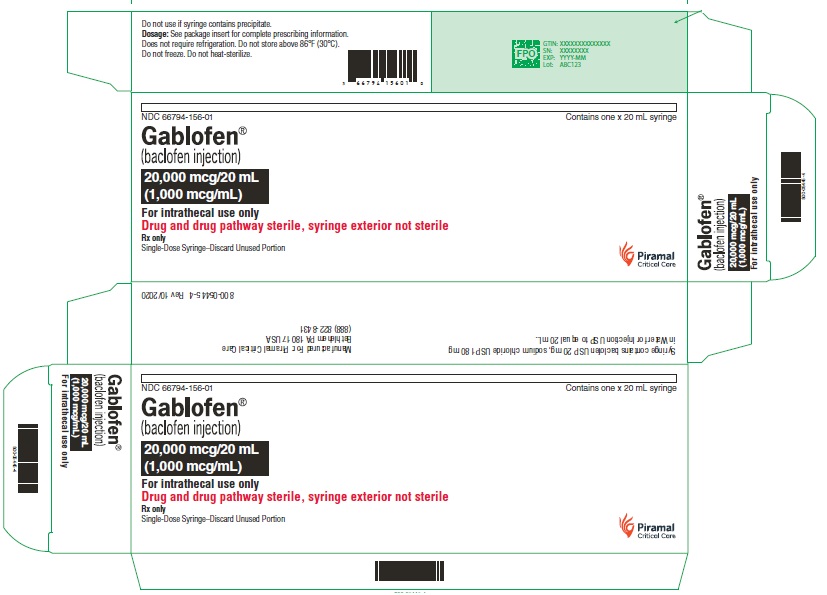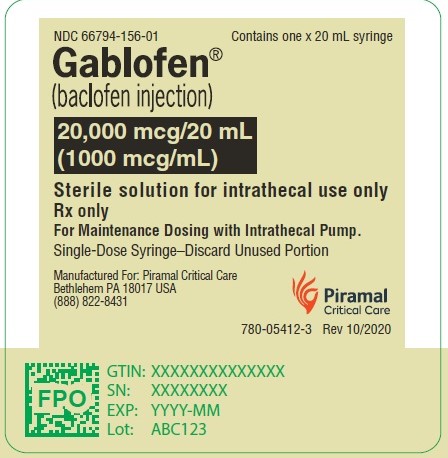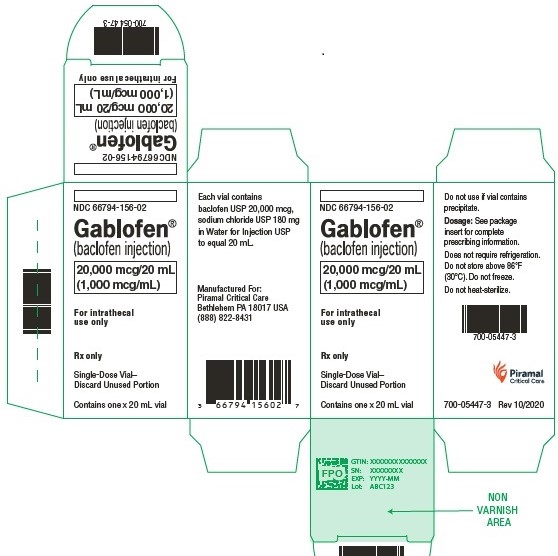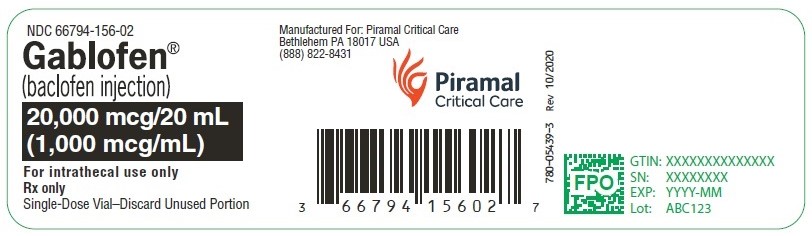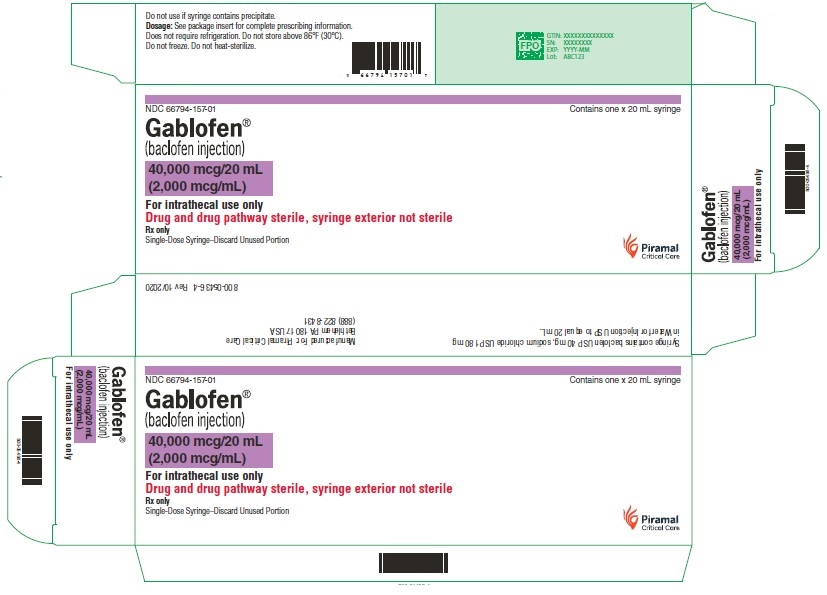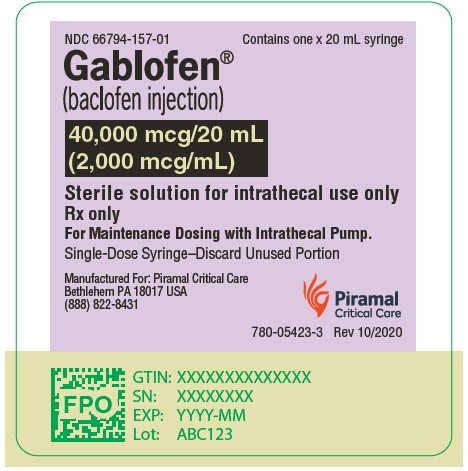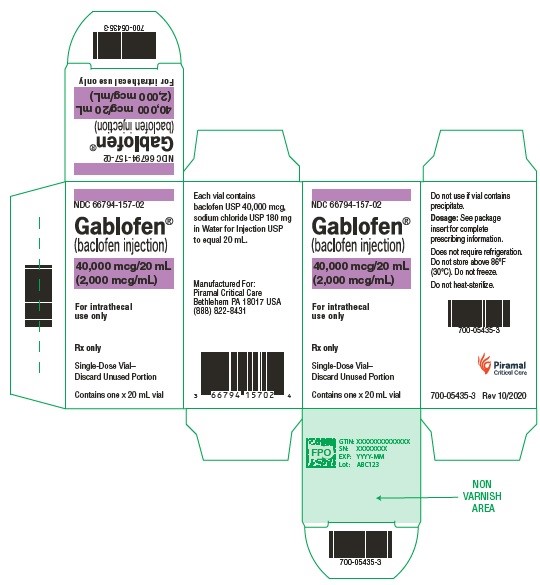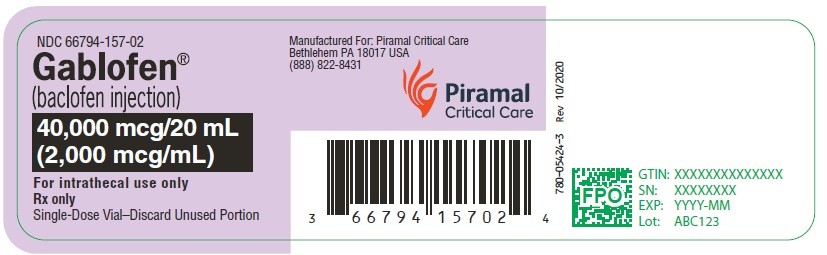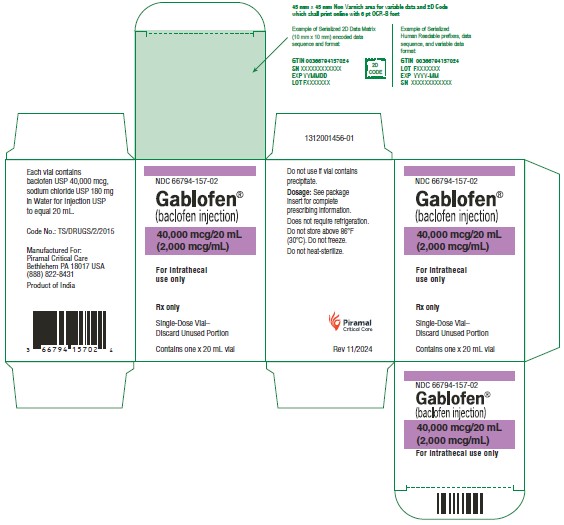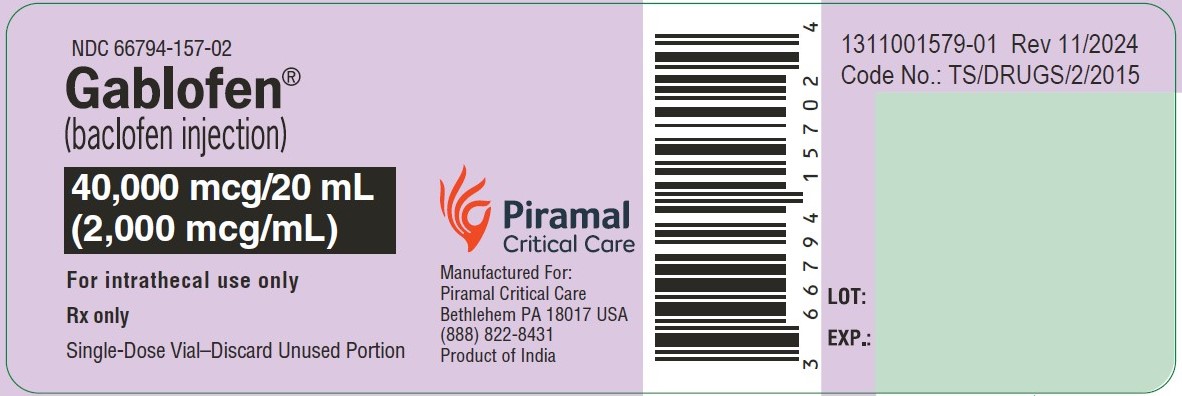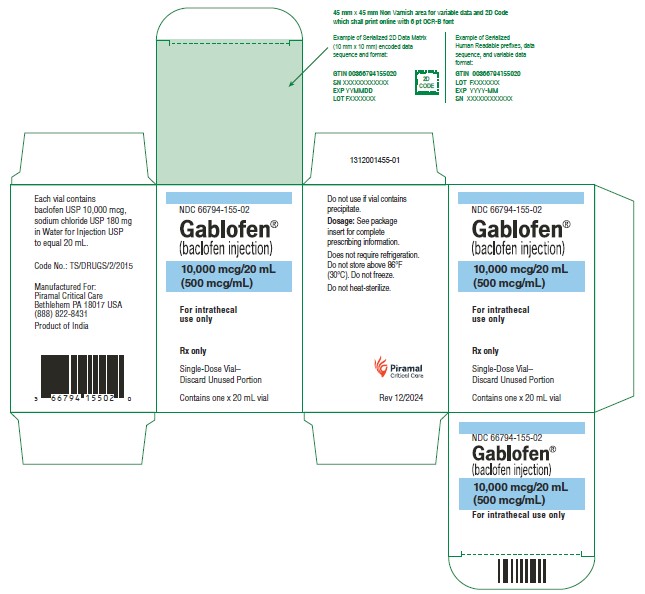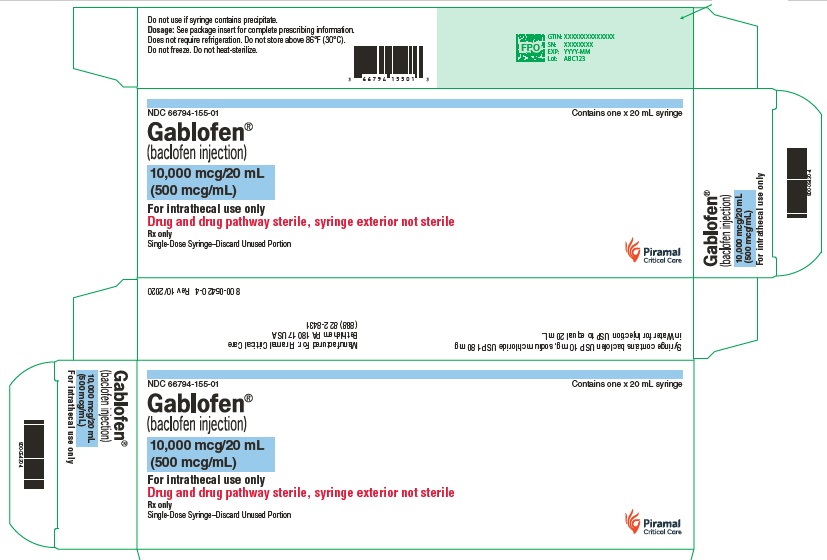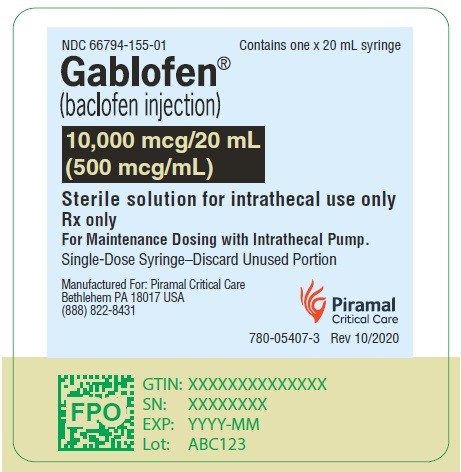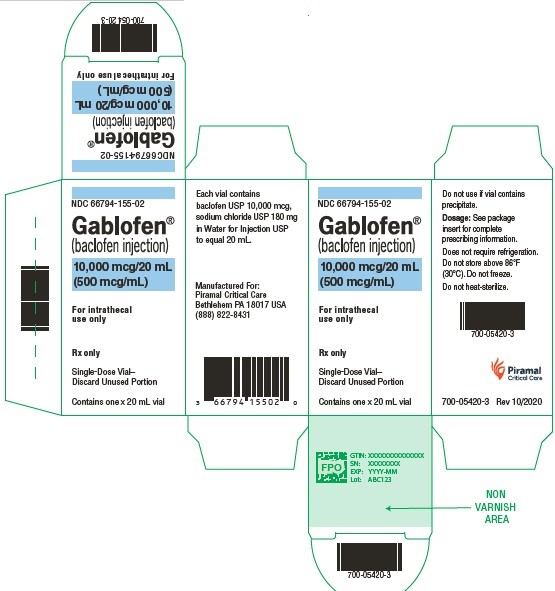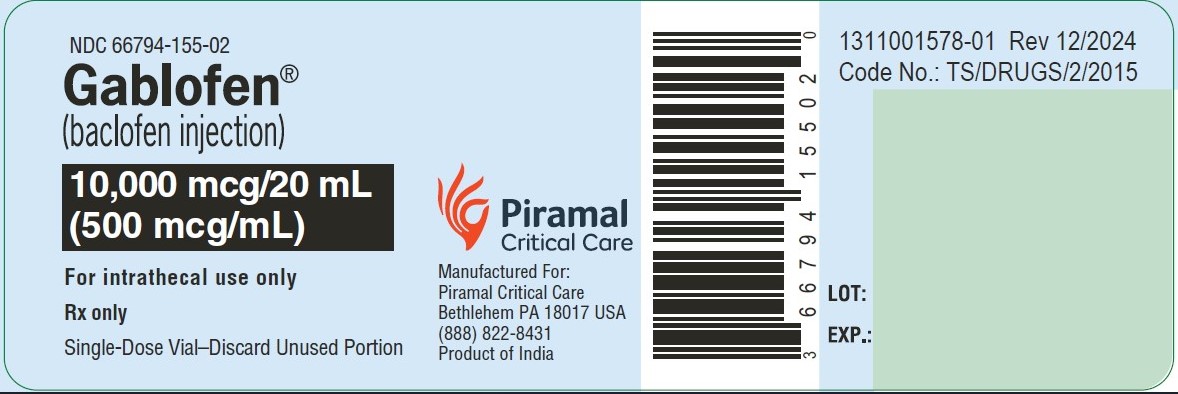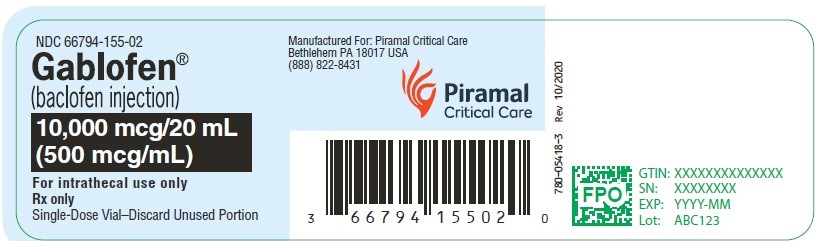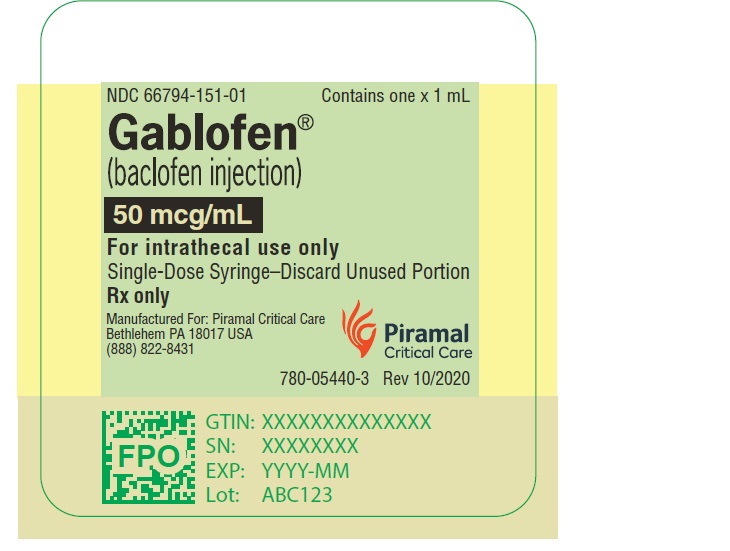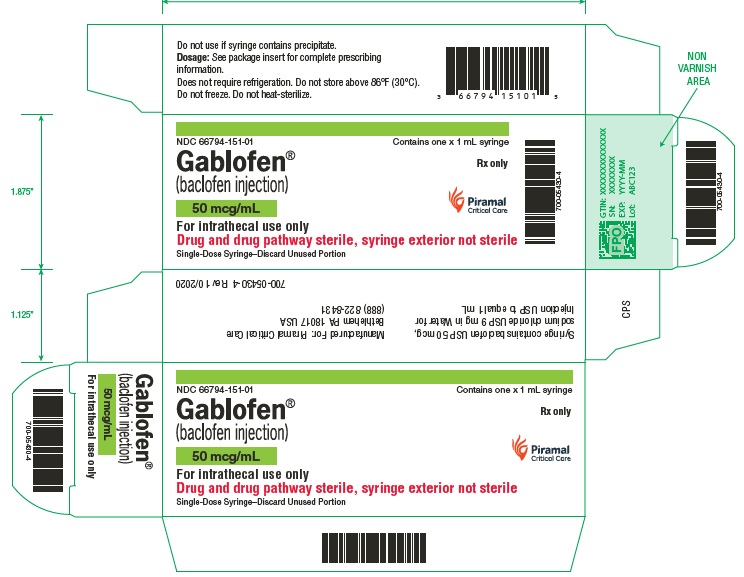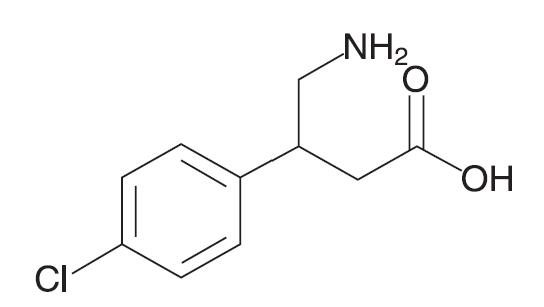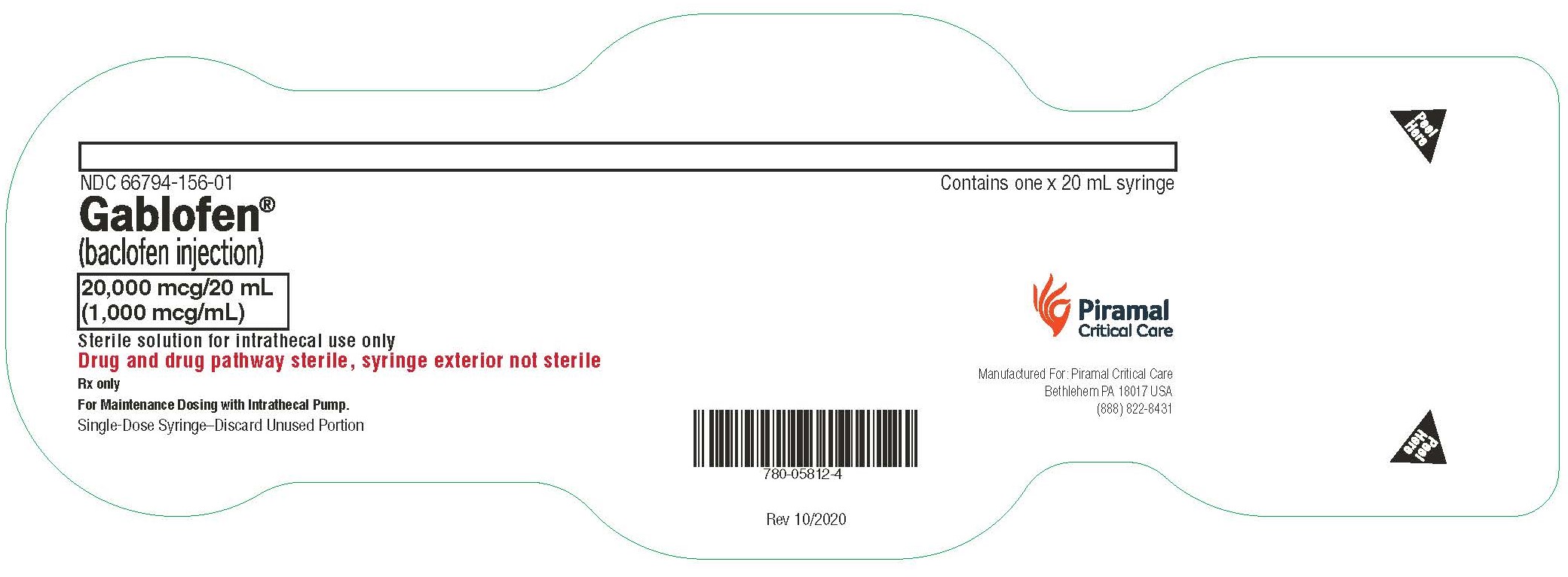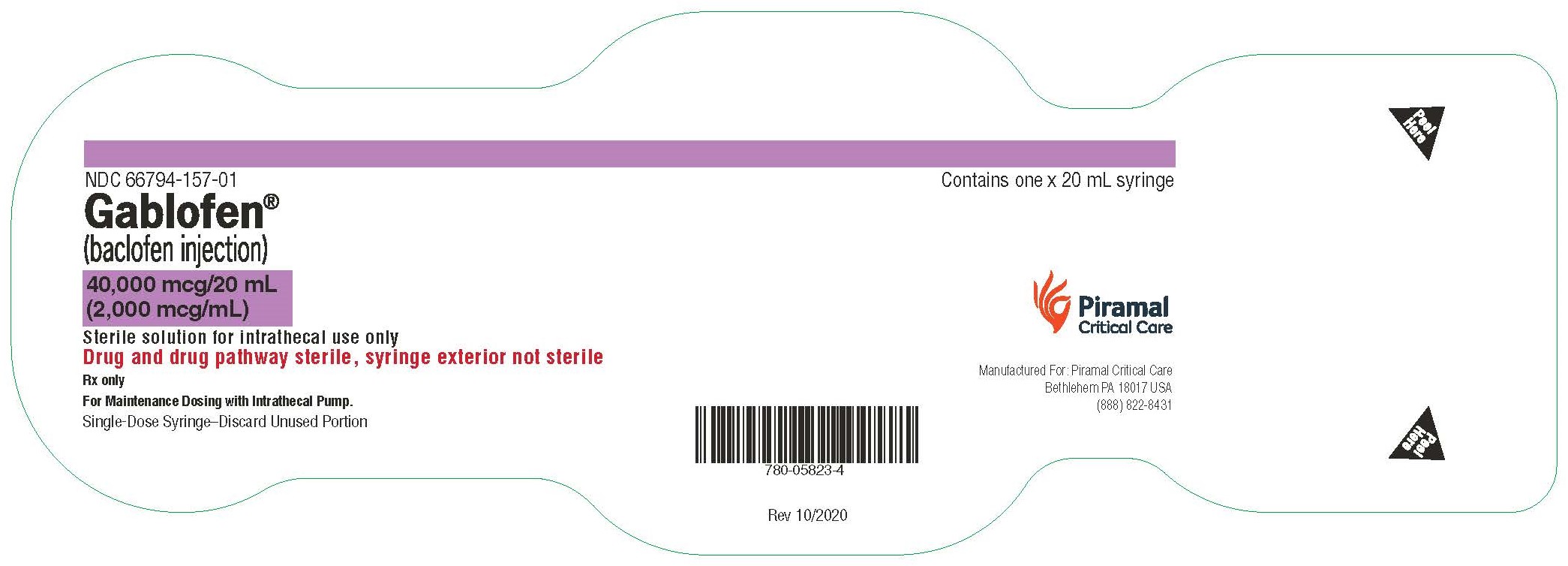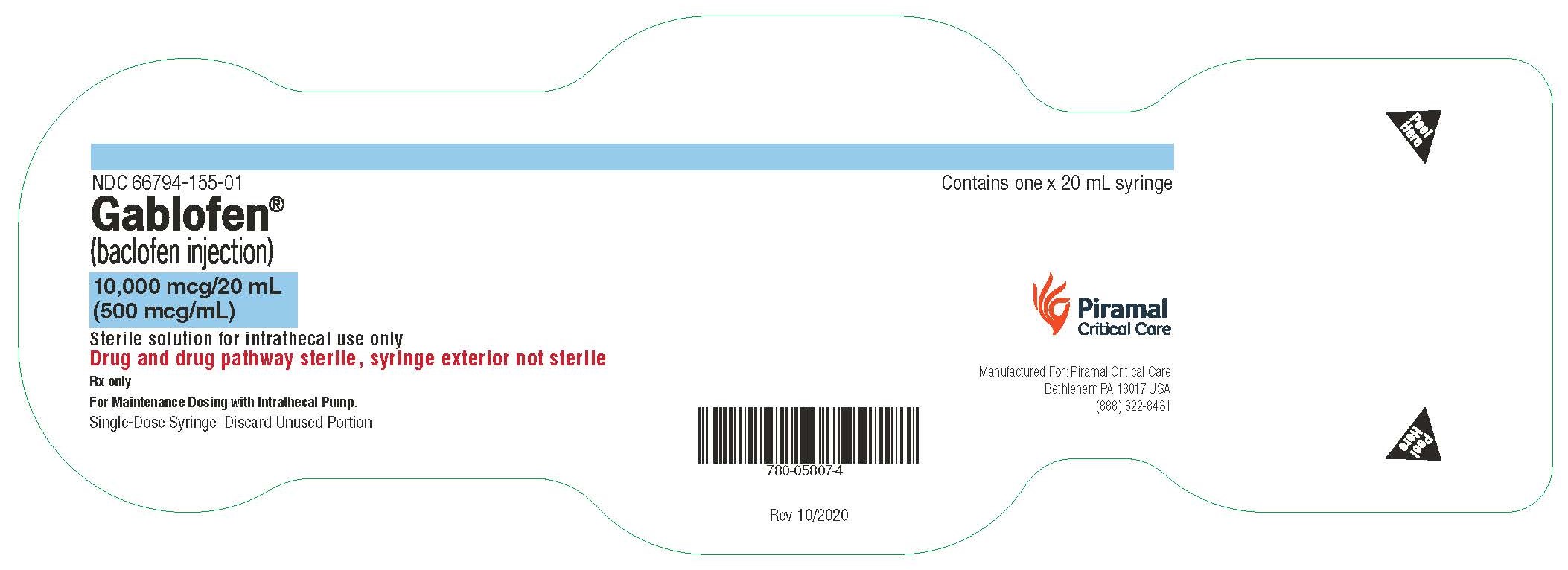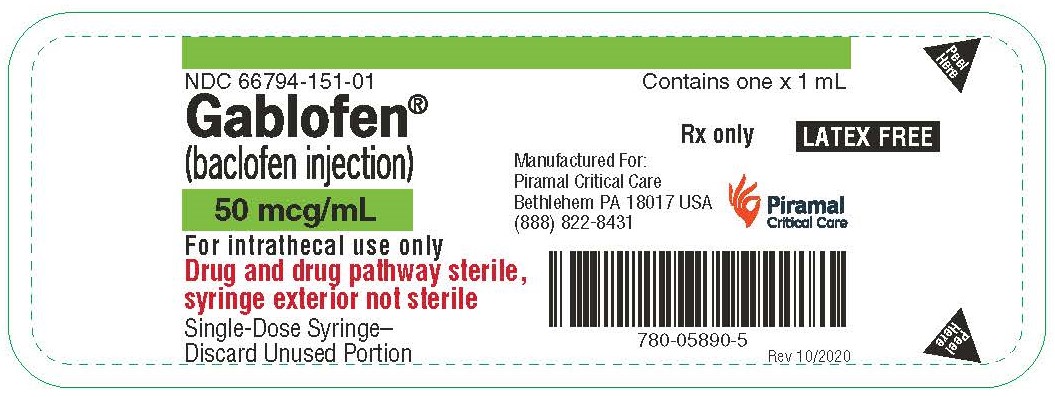 DRUG LABEL: Gablofen
NDC: 66794-151 | Form: INJECTION, SOLUTION
Manufacturer: Piramal Critical Care Inc
Category: prescription | Type: HUMAN PRESCRIPTION DRUG LABEL
Date: 20250923

ACTIVE INGREDIENTS: BACLOFEN 50 ug/1 mL
INACTIVE INGREDIENTS: SODIUM CHLORIDE; WATER

HIGHLIGHTS OF PRESCRIBING INFORMATION

These highlights do not include all the information needed to use GABLOFEN® safely and effectively. See full prescribing information for GABLOFEN.
GABLOFEN (baclofen injection), for intrathecal use
Initial U.S. Approval: 1992

BOXED WARNING

WARNING: DO NOT DISCONTINUE ABRUPTLY
See full prescribing information for complete boxed warning
Abrupt discontinuation of intrathecal baclofen, regardless of the cause, has resulted in sequelae that include high fever, altered mental status, exaggerated rebound spasticity, and muscle rigidity, that in rare cases has advanced to rhabdomyolysis, multiple organ-system failure and death.
Prevention of abrupt discontinuation of intrathecal baclofen requires careful attention to programming and monitoring of the infusion system, refill scheduling and procedures, and pump alarms. Patients and caregivers should be advised of the importance of keeping scheduled refill visits and should be educated on the early symptoms of baclofen withdrawal. Special attention should be given to patients at apparent risk (e.g., spinal cord injuries at T-6 or above, communication difficulties, history of withdrawal symptoms from oral or intrathecal baclofen). Consult the technical manual of the implantable infusion system for additional post-implant clinician and patient information. (5.4)

1 INDICATIONS AND USAGE

- GABLOFEN is a gamma-aminobutyric acid (GABA) ergic agonist indicated for use in the management of severe spasticity of cerebral or spinal origin in adult and pediatric patients age 4 years and above. (1)
- GABLOFEN should be reserved for patients unresponsive to oral baclofen therapy, or those who experience intolerable central nervous system side effects at effective doses. (1)
- Patients should first respond to a screening dose of intrathecal baclofen prior to consideration for long term infusion via an implantable pump. (1)
- Spasticity due to traumatic brain injury: wait at least one year after injury before considering GABLOFEN therapy. (1)

2 DOSAGE AND ADMINISTRATION

- GABLOFEN is intended for use by the intrathecal route in single bolus test doses (via spinal catheter or lumbar puncture) and, for chronic use in the Medtronic SynchroMed® Programmable Pump or other pumps labeled for intrathecal administration of GABLOFEN; Refer to the pump manufacturer's manual and follow the specific instructions and precautions for programming the pump and/or refilling the reservoir. (2.1)
- Screening: Patients who do not respond to a 100 mcg intrathecal bolus should not be considered for an implanted pump for chronic infusion. (2.2)
- Dose Titration: Spasticity may be necessary to sustain upright posture and balance in locomotion or may be useful to obtain optimal function and care. (2.5)
- Maintenance Therapy: Titrate patients individually; Lowest dose with an optimal response should be used, generally 300 mcg/day to 800 mcg/day for spasticity of spinal cord origin and 90 mcg/day to 700 mcg/day for spasticity of cerebral origin; Titrate GABLOFEN to maintain some degree of muscle tone and allow occasional spasms. (2.6)

3 DOSAGE FORMS AND STRENGTHS

Injection: 50 mcg/mL, 500 mcg/mL, 1,000 mcg/mL, and 2,000 mcg/mL (3)

4 CONTRAINDICATIONS

· Hypersensitivity to baclofen (4)

· Do not use GABLOFEN for intravenous, intramuscular, subcutaneous or epidural administration. (4)

5 WARNINGS AND PRECAUTIONS

· Do not directly inject GABLOFEN into the pump catheter access port, as this may cause a life-threatening overdose. (5.1)

· Potential for contamination due to non-sterile external surface of prefilled syringe. (5.2)

· Potentially life-threatening CNS depression, cardiovascular collapse, and/or respiratory failure; Resuscitative equipment and trained staff must be available during screening, dose titration, and refills (5.3)

· Overdose may cause drowsiness, lightheadedness, dizziness, somnolence, respiratory depression, seizures, rostral progression of hypotonia and loss of consciousness progressing to coma. (5.4)

· Possible exacerbation of psychotic disorders, schizophrenia or confusional states (5.6)

6 ADVERSE REACTIONS

· The most common adverse reactions in patients with spasticity of spinal origin were somnolence, dizziness, nausea, hypotension, headache, convulsions and hypotonia. (6.1)

· The most common adverse reactions in patients with spasticity of cerebral origin were agitation, constipation, somnolence, leukocytosis, chills, urinary retention and hypotonia. (6.2)

To report SUSPECTED ADVERSE REACTIONS, contact Piramal Critical Care, Inc. at 1-888-822-8431 or FDA at 1-800-FDA-1088 or www.fda.gov/medwatch.

7 DRUG INTERACTIONS

Combined use with morphine: hypotension and dyspnea (7)

8 USE IN SPECIFIC POPULATIONS

- Pregnancy: Based on animal data, may cause fetal harm (8.1)
- Pediatric use: Safety and effectiveness in pediatric patients below the age of 4 years have not been established (8.4)

See 17 for PATIENT COUNSELING INFORMATION

Revised: 12/2024

FULL PRESCRIBING INFORMATION

BOXED WARNING

WARNING: DO NOT DISCONTINUE ABRUPTLY
Abrupt discontinuation of intrathecal baclofen, regardless of the cause, has resulted in sequelae that include high fever, altered mental status, exaggerated rebound spasticity, and muscle rigidity, that in rare cases has advanced to rhabdomyolysis, multiple organ-system failure and death. Prevention of abrupt discontinuation of intrathecal baclofen requires careful attention to programming and monitoring of the infusion system, refill scheduling and procedures, and pump alarms. Patients and caregivers should be advised of the importance of keeping scheduled refill visits and should be educated on the early symptoms of baclofen withdrawal. Special attention should be given to patients at apparent risk (e.g., spinal cord injuries at T-6 or above, communication difficulties, history of withdrawal symptoms from oral or intrathecal baclofen). Consult the technical manual of the implantable infusion system for additional post-implant clinician and patient information [ see Warnings and Precautions (5.4)].

1 INDICATIONS AND USAGE

GABLOFEN is indicated for use in the management of severe spasticity in adult and pediatric patients age 4 years and above. Patients should first respond to a screening dose of intrathecal baclofen prior to consideration for long term infusion via an implantable pump. For spasticity of spinal cord origin, chronic infusion of GABLOFEN via an implantable pump should be reserved for patients unresponsive to oral baclofen therapy, or those who experience intolerable CNS side effects at effective doses. Patients with spasticity due to traumatic brain injury should wait at least one year after the injury before consideration of long term intrathecal baclofen therapy. GABLOFEN is intended for use by the intrathecal route in single bolus test doses (via spinal catheter or lumbar puncture) and, for chronic use, only with the Medtronic SynchroMed® Programmable Pump or other pumps labeled for intrathecal administration of GABLOFEN [see Clinical Studies (14)].

Prior to implantation of a device for chronic intrathecal infusion of GABLOFEN, patients must show a response to GABLOFEN in a screening trial [see Dosage and Administration (2.2)] .

2 DOSAGE AND ADMINISTRATION

2.1 Use Only in Medtronic SynchroMed® Programmable Pump (or other pumps labeled for intrathecal administration of GABLOFEN)

GABLOFEN is approved only for use with the Medtronic SynchroMed® Programmable Pump or other pumps labeled for intrathecal administration of GABLOFEN. Refer to the manufacturer’s manual for specific instructions and precautions for programming the pump and/or refilling the reservoir. It is important to select the appropriate refill kit for the pump used to administer GABLOFEN. GABLOFEN is not to be compounded with other medications.

2.2 Screening Phase

Prior to pump implantation and initiation of chronic infusion of GABLOFEN, patients must demonstrate a positive clinical response to a GABLOFEN bolus dose administered intrathecally in a screening trial. The screening trial employs GABLOFEN at a concentration of 50 mcg/mL. A 1 mL syringe (50 mcg/mL) is available for use in the screening trial. The screening procedure is as follows. An initial bolus containing 50 micrograms in a volume of 1 milliliter is administered into the intrathecal space by barbotage over a period of not less than one minute. The patient is observed over the ensuing 4 to 8 hours. A positive response consists of a significant decrease in muscle tone and/or frequency and/or severity of spasms. If the initial response is less than desired, a second bolus injection may be administered 24 hours after the first. The second screening bolus dose consists of 75 micrograms in 1.5 milliliters. Again, the patient should be observed for an interval of 4 to 8 hours. If the response is still inadequate, a final bolus screening dose of 100 micrograms in 2 milliliters may be administered 24 hours later.

Pediatric Patients

The starting screening dose for pediatric patients is the same as in adult patients, i.e., 50 mcg. However, for very small patients, a screening dose of 25 mcg may be tried first.

Patients who do not respond to a 100 mcg intrathecal bolus should not be considered candidates for an implanted pump for chronic infusion.

2.3 Preparation Information

Screening

Use the 1 mL screening syringe only (50 mcg/mL) for bolus injection into the subarachnoid space. For a 50 mcg bolus dose, use 1 mL of the screening syringe. Use 1.5 mL of 50 mcg/mL baclofen injection for a 75 mcg bolus dose. For the maximum screening dose of 100 mcg, use 2 mL of 50 mcg/mL baclofen injection (2 screening syringes).

Maintenance

The specific concentration that should be used depends upon the total daily dose required as well as the delivery rate of the pump. For patients who require concentrations other than 500 mcg/mL, 1,000 mcg/mL, or 2,000 mcg/mL, GABLOFEN must be diluted with sterile preservative free Sodium Chloride for Injection, USP.

2.4 Administration Information

Parenteral drug products should be inspected for particulate matter and discoloration prior to administration, whenever solution and container permit.

The external surface of GABLOFEN prefilled syringes (all strengths, including the 50 mcg/mL strength) are non-sterile. The use of GABLOFEN prefilled syringe in an aseptic setting (i.e., operating room) to fill sterile intrathecal pumps prior to implantation in patients is not recommended. For outpatient use, modify aseptic procedures to avoid contamination of sterile surfaces through contact with the non-sterile exterior of the GABLOFEN prefilled syringe when filling the pump reservoir [see Warnings and Precautions (5.2)].

Delivery Regimen

GABLOFEN is most often administered in a continuous infusion mode immediately following implant. For those patients implanted with programmable pumps who have achieved relatively satisfactory control on continuous infusion, further benefit may be attained using more complex schedules of GABLOFEN delivery. For example, patients who have increased spasms at night may require a 20% increase in their hourly infusion rate. Changes in flow rate should be programmed to start two hours before the time of desired clinical effect.

2.5 Dose Titration

Post-Implant Dose Titration Period

To determine the initial total daily dose of GABLOFEN following implant, the screening dose that gave a positive effect should be doubled and administered over a 24-hour period, unless the efficacy of the bolus dose was maintained for more than 8 hours, in which case the starting daily dose should be the screening dose delivered over a
24-hour period. No dose increases should be given in the first 24 hours (i.e., until the steady state is achieved). In most patients, it will be necessary to increase the dose gradually over time to maintain effectiveness; a sudden requirement for substantial dose escalation typically indicates a catheter complication (i.e., catheter kink or dislodgement).

Adult Patients with Spasticity of Spinal Cord Origin

After the first 24 hours, for adult patients, the daily dosage should be increased slowly by 10% to 30% increments and only once every 24 hours, until the desired clinical effect is achieved.

Adult Patients with Spasticity of Cerebral Origin

After the first 24 hours, the daily dose should be increased slowly by 5% to 15% only once every 24 hours, until the desired clinical effect is achieved.

Pediatric Patients

After the first 24 hours, the daily dose should be increased slowly by 5% to 15% only once every 24 hours, until the desired clinical effect is achieved. If there is not a substantive clinical response to increases in the daily dose, check for proper pump function and catheter patency. Patients must be monitored closely in a fully equipped and staffed environment during the screening phase and dose-titration period immediately following implant. Resuscitative equipment should be immediately available for use in case of life-threatening or intolerable side effects.

Additional Considerations Pertaining to Dosage Adjustment

Careful dose titration of GABLOFEN is needed when spasticity is necessary to sustain upright posture and balance in locomotion or whenever spasticity is used to obtain optimal function and care. It may be important to titrate the dose to maintain some degree of muscle tone and allow occasional spasms to: 1) help support circulatory function, 2) possibly prevent the formation of deep vein thrombosis, 3) optimize activities of daily living and ease of care.

Except in overdose related emergencies, the dose of GABLOFEN should ordinarily be reduced slowly if the drug is discontinued for any reason.

An attempt should be made to discontinue concomitant oral antispasticity medication to avoid possible overdose or adverse drug interactions, either prior to screening or following implant and initiation of chronic GABLOFEN infusion. Reduction and discontinuation of oral anti-spasmotics should be done slowly and with careful monitoring by the physician. Abrupt reduction or discontinuation of concomitant antispastics should be avoided.

2.6 Maintenance Therapy

Spasticity of Spinal Cord Origin Patients

The clinical goal is to maintain muscle tone as close to normal as possible, and to minimize the frequency and severity of spasms to the extent possible, without inducing intolerable side effects. Very often, the maintenance dose needs to be adjusted during the first few months of therapy while patients adjust to changes in lifestyle due to the alleviation of spasticity. During periodic refills of the pump, the daily dose may be increased by 10% to 40%, but no more than 40%, to maintain adequate symptom control. The daily dose may be reduced by 10% to 20% if patients experience side effects. Most patients require gradual increases in dose over time to maintain optimal response during chronic therapy. A sudden large requirement for dose escalation suggests a catheter complication (i.e., catheter kink or dislodgement).

Maintenance dosage for long term continuous infusion of intrathecal baclofen has ranged from 12 mcg/day to 2,003 mcg/day, with most patients adequately maintained on 300 micrograms to 800 micrograms per day. There is limited experience with daily doses greater than 1,000 mcg/day. Determination of the optimal GABLOFEN dose requires individual titration. The lowest dose with an optimal response should be used.

Spasticity of Cerebral Origin Patients

The clinical goal is to maintain muscle tone as close to normal as possible and to minimize the frequency and severity of spasms to the extent possible, without inducing intolerable side effects, or to titrate the dose to the desired degree of muscle tone for optimal functions. Very often the maintenance dose needs to be adjusted during the first few months of therapy while patients adjust to changes in lifestyle due to the alleviation of spasticity.

During periodic refills of the pump, the daily dose may be increased by 5% to 20%, but no more than 20%, to maintain adequate symptom control. The daily dose may be reduced by 10% to 20% if patients experience side effects. Many patients require gradual increases in dose over time to maintain optimal response during chronic therapy. A sudden large requirement for dose escalation suggests a catheter complication (i.e., catheter kink or dislodgement).

Maintenance dosage for long term continuous infusion of intrathecal baclofen has ranged from 22 mcg/day to 1,400 mcg/day, with most patients adequately maintained on 90 micrograms to 703 micrograms per day. In clinical trials, only 3 of 150 patients required daily doses greater than 1,000 mcg/day.

Pediatric Patients

Use same dosing recommendations for patients with spasticity of cerebral origin. Pediatric patients under 12 years seemed to require a lower daily dose in clinical trials. Average daily dose for patients under 12 years was 274 mcg/day, with a range of 24 mcg/day to 1,199 mcg/day. Dosage requirement for pediatric patients over 12 years does not seem to be different from that of adult patients. Determination of the optimal GABLOFEN dose requires individual titration. The lowest dose with an optimal response should be used.

Potential Need for Dose Adjustments in Chronic Use

During long term treatment, approximately 5% (28/627) of patients become refractory to increasing doses. There is not sufficient experience to make firm recommendations for tolerance treatment; however, this “tolerance” has been treated on occasion, in hospital, by a “drug holiday” consisting of the gradual reduction of intrathecal baclofen over a 2 to 4 week period and switching to alternative methods of spasticity management. After the “drug holiday,” intrathecal baclofen may be restarted at the initial continuous infusion dose.

3 DOSAGE FORMS AND STRENGTHS

GABLOFEN (baclofen injection) is a clear, colourless solution available as:

- Single-dose syringe containing 50 mcg/mL
- Single-dose syringes and vials of 10,000 mcg per 20 mL (500 mcg/mL)
- Single-dose syringes and vials of 20,000 mcg per 20 mL (1,000 mcg/mL)
- Single-dose syringes and vials of 40,000 mcg per 20 mL (2,000 mcg/mL)

4 CONTRAINDICATIONS

GABLOFEN is contraindicated in patients with a hypersensitivity to baclofen. Do not use GABLOFEN for intravenous, intramuscular, subcutaneous or epidural administration.

5 WARNINGS AND PRECAUTIONS

5.1 Risk of Life-Threatening Overdose During Pump Refills

Use extreme caution when filling the Medtronic SynchroMed® Programmable Pump which is equipped with an injection port that allows direct access to the intrathecal catheter. Direct injection into the catheter through the catheter access port may cause a life-threatening overdose.

Reservoir refilling must be performed by fully trained and qualified personnel following the directions provided by the pump manufacturer. Carefully calculate refill intervals to prevent depletion of the reservoir, as this would result in the return of severe spasticity and possibly symptoms of withdrawal.

Strict aseptic technique in filling is required to avoid bacterial contamination and serious infection. A period of observation appropriate to the clinical situation should follow each refill or manipulation of the drug reservoir.

5.2 Potential for Contamination due to Non-sterile External Surface of Prefilled Syringe

Although the drug solution and pathway in the GABLOFEN prefilled syringes are sterile, the external surface of the prefilled syringes (all strengths, including the 50 mcg/mL strength) are non-sterile. This has the potential to lead to contamination and consequent adverse reactions. The use of GABLOFEN prefilled syringe in an aseptic setting (e.g., operating room) to fill sterile intrathecal pumps prior to implantation in patients is not recommended, unless the external surface of the prefilled syringe is treated to ensure sterility. GABLOFEN supplied in vials may be used with conventional aseptic technique to fill intrathecal pumps prior to implantation. Procedures should also be put in place while refilling implantable intrathecal pumps in an outpatient setting to avoid contamination of sterile surfaces through contact with the non-sterile exterior of the GABLOFEN prefilled syringe.

5.3 Prescriber, Caregiver and Patient Training and Screening Procedure/Post-Implantation Environment

GABLOFEN is for use in single bolus intrathecal injections (via a catheter placed in the lumbar intrathecal space or injection by lumbar puncture) and in the implantable Medtronic SynchroMed® Programmable Pump or other pumps labeled for intrathecal administration of GABLOFEN. Because of the possibility of potentially life-threatening CNS depression, cardiovascular collapse, and/or respiratory failure, physicians must be adequately trained and educated in chronic intrathecal infusion therapy.

The pump system should not be implanted until the patient's response to bolus GABLOFEN injection is adequately evaluated. Evaluation (consisting of a screening procedure) requires that GABLOFEN be administered into the intrathecal space via a catheter or lumbar puncture [see Dosage and Administration (2.2)]. Because of the risks associated with the screening procedure and the adjustment of dosage following pump implantation, these phases must be conducted in a medically supervised and adequately equipped environment following the instructions outlined in the Dosage and Administration section [see Dosage and Administration (2.2 and 2.5)] .

Resuscitative equipment should be available.

Following surgical implantation of the pump, particularly during the initial phases of pump use, the patient should be monitored closely until it is certain that the patient's response to the infusion is acceptable and reasonably stable.

On each occasion that the dosing rate of the pump and/or the concentration of GABLOFEN in the reservoir is adjusted, close medical monitoring is required until it is certain that the patient's response to the infusion is acceptable and reasonably stable.

It is mandatory that the patient, all patient caregivers, and the physicians responsible for the patient receive adequate information regarding the risks of this mode of treatment. All medical personnel and caregivers should be instructed in 1) the signs and symptoms of overdose, 2) procedures to be followed in the event of overdose and 3) proper home care of the pump and insertion site.

5.4 Overdose

Signs of overdose may appear suddenly or insidiously. Acute massive overdose may present as coma. Less sudden and/or less severe forms of overdose may present with signs of drowsiness, lightheadedness, dizziness, somnolence, respiratory depression, seizures, rostral progression of hypotonia and loss of consciousness progressing to coma. Should overdose appear likely, the patient should be taken immediately to a hospital for assessment and emptying of the pump reservoir. In cases reported to date, overdose has generally been related to pump malfunction or dosing error [ see Overdosage (10)]

Extreme caution must be used when filling the implantable pump.

Medtronic SynchroMed® Programmable Pump should only be refilled through the reservoir refill septum. The Medtronic SynchroMed® Programmable Pump is also equipped with a catheter access port that allows direct access to the intrathecal catheter. Direct injection into this catheter access port may cause a life-threatening overdose.

5.5 Withdrawal

Abrupt withdrawal of intrathecal baclofen, regardless of the cause, has resulted in sequelae that included high fever, altered mental status, exaggerated rebound spasticity and muscle rigidity that in rare cases progressed to rhabdomyolysis, multiple organ-system failure, and death. In the first 9 years of post-marketing experience, 27 cases of withdrawal temporally related to the cessation of baclofen therapy were reported; six patients died. In most cases, symptoms of withdrawal appeared within hours to a few days following interruption of baclofen therapy. Common reasons for abrupt interruption of intrathecal baclofen therapy included malfunction of the catheter (especially disconnection), low volume in the pump reservoir, and end of pump battery life; human error may have played a causal or contributing role in some cases. Cases of intrathecal mass at the tip of the implanted catheter leading to withdrawal symptoms have also been reported, most of them involving pharmacy compounded analgesic admixtures [see Warnings and Precautions (5.10)].

Prevention of abrupt discontinuation of intrathecal baclofen requires careful attention to programming and monitoring of the infusion system, refill scheduling and procedures, and pump alarms. Patients and caregivers should be advised of the importance of keeping scheduled refill visits and should be educated on the early symptoms of baclofen withdrawal.

All patients receiving intrathecal baclofen therapy are potentially at risk for withdrawal. Early symptoms of baclofen withdrawal may include return of baseline spasticity, pruritus, hypotension, and paresthesias. Some clinical characteristics of the advanced intrathecal baclofen withdrawal syndrome may resemble autonomic dysreflexia, infection (sepsis), malignant hyperthermia, neuroleptic-malignant syndrome, or other conditions associated with a hypermetabolic state or widespread rhabdomyolysis.

Rapid, accurate diagnosis and treatment in an emergency-room or intensive-care setting are important in order to prevent the potentially life-threatening central nervous system and systemic effects of intrathecal baclofen withdrawal. The suggested treatment for intrathecal baclofen withdrawal is the restoration of intrathecal baclofen at or near the same dosage as before therapy was interrupted. However, if restoration of intrathecal delivery is delayed, treatment with GABA-ergic agonist drugs such as oral or enteral baclofen, or oral, enteral, or intravenous benzodiazepines may prevent potentially fatal sequelae. Oral or enteral baclofen alone should not be relied upon to halt the progression of intrathecal baclofen withdrawal.

Seizures have been reported during overdose and with withdrawal from intrathecal baclofen as well as in patients maintained on therapeutic doses of intrathecal baclofen.

5.6 Possible Exacerbation of Psychotic Disorders, Schizophrenia, or Confusional States

Patients suffering from psychotic disorders, schizophrenia, or confusional states should be treated cautiously with GABLOFEN and kept under careful surveillance, because exacerbations of these conditions have been observed with oral administration.

5.7 Fatalities

Spasticity of Spinal Cord Origin

There were 16 deaths reported among the 576 U.S. patients treated with intrathecal baclofen in pre- and post-marketing studies evaluated as of December 1992. Because these patients were treated under uncontrolled clinical settings, it is impossible to determine definitively what role, if any, intrathecal baclofen played in their deaths. As a group, the patients who died were relatively young (mean age was 47 with a range from 25 to 63), but the majority suffered from severe spasticity of many years duration, were nonambulatory, had various medical complications such as pneumonia, urinary tract infections, and decubiti, and/or had received multiple concomitant medications. A case-by-case review of the clinical course of the 16 patients who died failed to reveal any unique signs, symptoms, or laboratory results that would suggest that treatment with intrathecal baclofen caused their deaths. Two patients, however, did suffer sudden and unexpected death within 2 weeks of pump implantation and one patient died unexpectedly after screening.

One patient, a 44 year-old male with Multiple Sclerosis, died in hospital on the second day following pump implantation. An autopsy demonstrated severe fibrosis of the coronary conduction system. A second patient, a 52 year-old woman with MS and a history of an inferior wall myocardial infarction, was found dead in bed 12 days after pump implantation, 2 hours after having had documented normal vital signs. An autopsy revealed pulmonary congestion and bilateral pleural effusions. It is impossible to determine whether intrathecal baclofen contributed to these deaths. The third patient underwent three baclofen screening trials. His medical history included spinal cord injury, aspiration pneumonia, septic shock, disseminated intravascular coagulopathy, severe metabolic acidosis, hepatic toxicity, and status epilepticus. Twelve days after screening (he was not implanted), he again experienced status epilepticus with subsequent significant neurological deterioration. Based upon prior instruction, extraordinary resuscitative measures were not pursued and the patient died.

Spasticity of Cerebral Origin

There were three deaths occurring among the 211 patients treated with intrathecal baclofen in pre-marketing studies as of March 1996. These deaths were not attributed to the therapy.

5.8 Use with Caution in Patients with a History of Autonomic Dysreflexia

GABLOFEN should be used with caution in patients with a history of autonomic dysreflexia. The presence of nociceptive stimuli or abrupt withdrawal of GABLOFEN may cause an autonomic dysreflexic episode.

5.9 Infections

Patients should be infection-free prior to the screening trial with GABLOFEN because the presence of a systemic infection may interfere with an assessment of the patient's response to bolus GABLOFEN. Patients should be infection-free prior to implantation of the pump because the presence of infection may increase the risk of surgical complications. Moreover, a systemic infection may complicate dosing.

5.10 Drowsiness

Drowsiness has been reported in patients on intrathecal baclofen. Patients should be cautioned regarding the operation of automobiles or other dangerous machinery, and activities made hazardous by decreased alertness. Patients should also be cautioned that the central nervous system depressant effects of intrathecal baclofen may be additive to those of alcohol and other CNS depressants.

5.11 Intrathecal Mass Formation

Cases of intrathecal mass at the tip of the implanted catheter have been reported, most of them involving pharmacy compounded analgesic admixtures. The most frequent symptoms associated with intrathecal mass are: 1) decreased therapeutic response (worsening spasticity, return of spasticity when previously well controlled, withdrawal symptoms, poor response to escalating doses, or frequent or large dosage increases), 2) pain, 3) neurological deficit/dysfunction. Clinicians should monitor patients on intraspinal therapy carefully for any new neurological signs or symptoms. In patients with new neurological signs or symptoms suggestive of an intrathecal mass, consider a neurosurgical consultation, since many of the symptoms of inflammatory mass are not unlike the symptoms experienced by patients with severe spasticity from their disease. In some cases, performance of an imaging procedure may be appropriate to confirm or rule-out the diagnosis of an intrathecal mass.

5.12 Ovarian Cysts

A dose-related increase in incidence of ovarian cysts was observed in female rats treated chronically with oral baclofen. Ovarian cysts have been found by palpation in about 4% of the multiple sclerosis patients who were treated with oral baclofen for up to one year. In most cases these cysts disappeared spontaneously while patients continued to receive the drug. Ovarian cysts are estimated to occur spontaneously in approximately 1% to 5% of the normal female population.

6 ADVERSE REACTIONS

6.1 Spasticity of Spinal Cord Origin

Most Common Adverse Reactions in Patients with Spasticity of Spinal Origin
In pre- and post-marketing clinical trials, the most common adverse reactions associated with use of intrathecal baclofen which were not seen at an equivalent incidence among placebo-treated patients were: somnolence, dizziness, nausea, hypotension, headache, convulsions and hypotonia.

Adverse Reactions Associated with Discontinuation of Treatment
8/474 patients with spasticity of spinal cord origin receiving long term infusion of intrathecal baclofen in pre- and post-marketing clinical studies in the U.S. discontinued treatment due to adverse reactions. These include: pump pocket infections (3), meningitis (2), wound dehiscence (1), gynecological fibroids (1) and pump overpressurization (1) with unknown, if any, sequela. Eleven patients who developed coma secondary to overdose had their treatment temporarily suspended, but all were subsequently re-started and were not, therefore, considered to be true discontinuations.

Fatalities - [see Warnings and Precautions (5.6)].

Incidence in Controlled Trials

Experience with intrathecal baclofen obtained in parallel, placebo-controlled, randomized studies provides only a limited basis for estimating the incidence of adverse reactions because the studies were of very brief duration (up to three days of infusion) and involved only a total of 63 patients. The following events occurred among the 31 patients receiving intrathecal baclofen in two randomized, placebo-controlled trials: hypotension (2), dizziness (2), headache (2), dyspnea (1). No adverse reactions were reported among the 32 patients receiving placebo in these studies.

Events Observed during the Pre- and Post-marketing Evaluation of Intrathecal Baclofen

Adverse events associated with the use of intrathecal baclofen reflect experience gained with 576 patients followed prospectively in the United States. They received intrathecal baclofen for periods of one day (screening) (N=576) to over eight years (maintenance) (N=10). The usual screening bolus dose administered prior to pump implantation in these studies was typically 50 mcg. The maintenance dose ranged from 12 mcg to 2,003 mcg per day. Because of the open, uncontrolled nature of the experience, a causal linkage between events observed and the administration of intrathecal baclofen cannot be reliably assessed in many cases and many of the adverse reactions reported are known to occur in association with the underlying conditions being treated. Nonetheless, many of the more commonly reported reactions — hypotonia, somnolence, dizziness, paresthesia, nausea/vomiting and headache — appear clearly drug-related.
Adverse experiences reported during all U.S. studies (both controlled and uncontrolled) are shown in Table 1. Eight of 474 patients who received chronic infusion via implanted pumps had adverse experiences which led to a discontinuation of long term treatment in the pre- and post-marketing studies.
Table 1: Most Common (≥1%) Adverse Reactions in Patients with Spasticity of Spinal Origin in Prospectively Monitored Clinical Trials

Adverse Reactions | Percent N=576 Screening | Percent N=474 Titration† | Percent N=430 Maintenance‡
Hypotonia | 5.4 | 13.5 | 25.3
Somnolence | 5.7 | 5.9 | 20.9
Dizziness | 1.7 | 1.9 | 7.9
Paresthesia | 2.4 | 2.1 | 6.7
Nausea and Vomiting | 1.6 | 2.3 | 5.6
Headache | 1.6 | 2.5 | 5.1
Constipation | 0.2 | 1.5 | 5.1
Convulsion | 0.5 | 1.3 | 4.7
Urinary Retention | 0.7 | 1.7 | 1.9
Dry Mouth | 0.2 | 0.4 | 3.3
Accidental Injury | 0.0 | 0.2 | 3.5
Asthenia | 0.7 | 1.3 | 1.4
Confusion | 0.5 | 0.6 | 2.3
Death | 0.2 | 0.4 | 3.0
Pain | 0.0 | 0.6 | 3.0
Speech Disorder | 0.0 | 0.2 | 3.5
Hypotension | 1.0 | 0.2 | 1.9
Ambylopia | 0.5 | 0.2 | 2.3
Diarrhea | 0.0 | 0.8 | 2.3
Hypoventilation | 0.2 | 0.8 | 2.1
Coma | 0.0 | 1.5 | 0.9
Impotence | 0.2 | 0.4 | 1.6
Peripheral Edema | 0.0 | 0.0 | 2.3
Urinary Incontinence | 0.0 | 0.8 | 1.4
Insomnia | 0.0 | 0.4 | 1.6
Anxiety | 0.2 | 0.4 | 0.9
Depression | 0.0 | 0.0 | 1.6
Dypsnea | 0.3 | 0.0 | 1.2
Fever | 0.5 | 0.2 | 0.7
Pneumonia | 0.2 | 0.2 | 1.2
Urinary Frequency | 0.0 | 0.6 | 0.9
Urticaria | 0.2 | 0.2 | 1.2
Anorexia | 0.0 | 0.4 | 0.9
Diplopia | 0.0 | 0.4 | 0.9
Dysautonomia | 0.2 | 0.2 | 0.9
Hallucinations | 0.3 | 0.4 | 0.5
Hypertension | 0.2 | 0.6 | 0.5

* Following administration of test bolus † Two month period following implant
‡ Beyond two months following implant
N=Total number of patients entering each period
%=% of patients evaluated

In addition to the more common (1% or more) adverse reactions reported in the prospectively followed 576 domestic patients in pre- and post-marketing studies, experience from an additional 194 patients exposed to intrathecal baclofen from foreign studies has been reported. The following adverse reactions, not described in the table, and arranged in decreasing order of frequency, and classified by body system, were reported:
Nervous System: Abnormal gait, thinking abnormal, tremor, amnesia, twitching, vasodilatation, cerebrovascular accident, nystagmus, personality disorder, psychotic depression, cerebral ischemia, emotional lability, euphoria, hypertonia, ileus, drug dependence, incoordination, paranoid reaction and ptosis.
Digestive System: Flatulence, dysphagia, dyspepsia and gastroenteritis.
Cardiovascular: Postural hypotension, bradycardia, palpitations, syncope, arrhythmia ventricular, deep thrombophlebitis, pallor and tachycardia.
Respiratory: Respiratory disorder, aspiration pneumonia, hyperventilation, pulmonary embolus and rhinitis.
Urogenital: Hematuria and kidney failure.
Skin and Appendages: Alopecia and sweating.
Metabolic and Nutritional Disorders: Weight loss, albuminuria, dehydration and hyperglycemia.
Special Senses: Abnormal vision, abnormality of accommodation, photophobia, taste loss and tinnitus.
Body as a Whole: Suicide, lack of drug effect, abdominal pain, hypothermia, neck rigidity, chest pain, chills, face edema, flu syndrome and overdose.
Hemic and Lymphatic System: Anemia.

6.2 Spasticity of Cerebral Origin
Most Common Adverse Reactions
In pre-marketing clinical trials, the most common adverse reactions associated with use of intrathecal baclofen which were not seen at an equivalent incidence among placebo-treated patients included: agitation, constipation, somnolence, leukocytosis, chills, urinary retention and hypotonia.
Adverse Reactions Associated with Discontinuation of Treatment
Nine of 211 patients receiving intrathecal baclofen in pre-marketing clinical studies in the U.S. discontinued long-term infusion due to adverse reactions associated with intrathecal therapy.
The nine adverse reactions leading to discontinuation were: infection (3), CSF leaks (2), meningitis (2), drainage (1), and unmanageable trunk control (1).
Fatalities
Three deaths, none of which were attributed to intrathecal baclofen, were reported in patients in clinical trials involving patients with spasticity of cerebral origin. See Warnings on other deaths reported in spinal spasticity patients.
Incidence in Controlled Trials
Experience with intrathecal baclofen obtained in parallel, placebo-controlled, randomized studies provides only a limited basis for estimating the incidence of adverse reactions because the studies involved a total of 62 patients exposed to a single 50 mcg intrathecal bolus. The following adverse reactions occurred among the 62 patients receiving intrathecal baclofen in two randomized, placebo-controlled trials involving cerebral palsy and head injury patients, respectively: agitation, constipation, somnolence, leukocytosis, nausea, vomiting, nystagmus, chills, urinary retention, and hypotonia.
Events Observed during the Pre-marketing Evaluation of Intrathecal Baclofen
Adverse events associated with the use of intrathecal baclofen reflect experience gained with a total of 211 U.S. patients with spasticity of cerebral origin, of whom 112 were pediatric patients (under age 16 at enrollment). They received intrathecal baclofen for periods of one day (screening) (N=211) to 84 months (maintenance) (N=1). The usual screening bolus dose administered prior to pump implantation in these studies was 50 mcg to 75 mcg. The maintenance dose ranged from 22 mcg to 1,400 mcg per day. Doses used in this patient population for long-term infusion are generally lower than those required for patients with spasticity of spinal cord origin.
Because of the open, uncontrolled nature of the experience, a causal linkage between events observed and the administration of intrathecal baclofen cannot be reliably assessed in many cases. Nonetheless, many of the more commonly reported reactions — somnolence, dizziness, headache, nausea, hypotension, hypotonia and coma — appear clearly drug-related.
The most frequent (≥1%) adverse reactions reported during all clinical trials are shown in Table 2. Nine patients discontinued long term treatment due to adverse reactions.
Table 2: Most Common (≥1%) Adverse Reactions in Patients with Spasticity of Cerebral Origin

Adverse Reactions | Percent N=211 Screening* | Percent N=153 Titration† | Percent N=150 Maintenance‡
Hypotonia | 2.4 | 14.4 | 34.7
Somnolence | 7.6 | 10.5 | 18.7
Headache | 6.6 | 7.8 | 10.7
Nausea and Vomiting | 6.6 | 10.5 | 4.0
Vomiting | 6.2 | 8.5 | 4.0
Urinary Retention | 0.9 | 6.5 | 8.0
Convulsion | 0.9 | 3.3 | 10.0
Dizziness | 2.4 | 2.6 | 8.0
Nausea | 1.4 | 3.3 | 7.3
Hypoventilation | 1.4 | 1.3 | 4.0
Hypertonia | 0.0 | 0.7 | 6.0
Paresthesia | 1.9 | 0.7 | 3.3
Hypotension | 1.9 | 0.7 | 2.0
Increased Salivation | 0.0 | 2.6 | 2.7
Back Pain | 0.9 | 0.7 | 2.0
Constipation | 0.5 | 1.3 | 2.0
Pain | 0.0 | 0.0 | 4.0
Pruritus | 0.0 | 0.0 | 4.0
Diarrhea | 0.5 | 0.7 | 2.0
Peripheral Edema | 0.0 | 0.0 | 3.3
Thinking Abnormal | 0.5 | 1.3 | 0.7
Agitation | 0.5 | 0.0 | 1.3
Asthenia | 0.0 | 0.0 | 2.0
Chills | 0.5 | 0.0 | 1.3
Coma | 0.5 | 0.0 | 1.3
Dry Mouth | 0.5 | 0.0 | 1.3
Pneumonia | 0.0 | 0.0 | 2.0
Speech Disorder | 0.5 | 0.7 | 0.7
Tremor | 0.5 | 0.0 | 1.3
Urinary Incontinence | 0.0 | 0.0 | 2.0
Urination Impaired | 0.0 | 0.0 | 2.0

* Following administration of test bolus

† Two month period following implant
‡ Beyond two months following implant
N=Total number of patients entering each period. 211 patients received drug; (1 of 212) received placebo only
The more common (1% or more) adverse reactions reported in the prospectively followed 211 patients exposed to intrathecal baclofen have been reported. In the total cohort, the following adverse reactions, not described in Table 2, and arranged in decreasing order of frequency, and classified by body system, were reported:
Nervous System: Akathisia, ataxia, confusion, depression, opisthotonos, amnesia, anxiety, hallucinations, hysteria, insomnia, nystagmus, personality disorder, reflexes decreased, and vasodilitation.
Digestive System: Dysphagia, fecal incontinence, gastrointestinal hemorrhage and tongue disorder.
Cardiovascular: Bradycardia.
Respiratory: Apnea, dyspnea and hyperventilation.
Urogenital: Abnormal ejaculation, kidney calculus, oliguria and vaginitis.
Skin and Appendages: Rash, sweating, alopecia, contact dermatitis and skin ulcer.
Special Senses: Abnormality of accommodation.
Body as a Whole: Death, fever, abdominal pain, carcinoma, malaise and hypothermia.
Hemic and Lymphatic System: Leukocytosis and petechial rash.

7 DRUG INTERACTIONS

There is inadequate systematic experience with the use of intrathecal baclofen in combination with other medications to predict specific drug-drug interactions. Interactions attributed to the combined use of GABLOFEN and epidural morphine include hypotension and dyspnea.

8 USE IN SPECIFIC POPULATIONS

.

8.1 Pregnancy

Risk Summary

There are no adequate data on the developmental risk associated with the use of GABLOFEN in pregnant women.

In animal studies, oral administration of baclofen to pregnant rats produced an increase in fetal malformations (see Data). There are no animal data on developmental risk associated with baclofen administered via continuous intrathecal infusion.

The background risk of major birth defects and miscarriage for the indicated population is unknown. In the U.S. general population, the estimated background risk of major birth defects and miscarriage in clinically recognized pregnancies is 2 to 4% and 15 to 20%, respectively.

Data

Animal Data

Baclofen given orally to pregnant rats has been shown to increase the incidence of omphaloceles (ventral hernias) in fetuses at a dose associated with maternal toxicity. This abnormality was not seen in mice or rabbits.

8.2 Lactation

Risk Summary

There is insufficient information regarding levels of baclofen in milk of nursing mothers receiving GABLOFEN. There are no adequate data on the effects of GABLOFEN on the breastfed infant or on milk production. At recommended oral doses, baclofen is present in human milk and withdrawal symptoms can occur in breastfed infants when maternal administration of baclofen is stopped or when breastfeeding is stopped.

The developmental and health benefits of breastfeeding should be considered along with the mother’s clinical need for GABLOFEN and any potential adverse effects on the breastfed infant from GABLOFEN or from the underlying maternal condition.

8.4 Pediatric Use

Children should be of sufficient body mass to accommodate the implantable pump for chronic infusion. Please consult pump manufacturer's manual for specific recommendations.

Safety and effectiveness in pediatric patients below the age of 4 have not been established.

10 OVERDOSAGE

Special attention must be given to recognizing the signs and symptoms of overdosage, especially during the initial screening and dose-titration phase of treatment, but also during re-introduction of GABLOFEN after a period of interruption in therapy.

Symptoms of Intrathecal Baclofen Overdose

Drowsiness, lightheadedness, dizziness, somnolence, respiratory depression, seizures, rostral progression of hypotonia and loss of consciousness progressing to coma of up to 72 hours duration. In most cases reported, coma was reversible without sequelae after drug was discontinued. Symptoms of intrathecal baclofen overdose were reported in a sensitive adult patient after receiving a 25 mcg intrathecal bolus.

Treatment Suggestions for Overdose

There is no specific antidote for treating overdoses of GABLOFEN; however, the following steps should ordinarily be undertaken:

1) Residual intrathecal baclofen solution should be removed from the pump as soon as possible.

2) Patients with respiratory depression should be intubated if necessary, until the drug is eliminated.

Anecdotal reports suggest that intravenous physostigmine may reverse central side effects, notably drowsiness and respiratory depression. Caution in administering physostigmine is advised, however, because its use has been associated with the induction of seizures and bradycardia.

Physostigmine Doses for Adult Patients

Administer 2 mg of physostigmine intramuscularly or intravenously at a slow controlled rate of no more than 1 mg per minute. Dosage may be repeated if life-threatening signs, such as arrhythmia, convulsions or coma occur.

Physostigmine Doses for Pediatric Patients

Administer 0.02 mg/kg physostigmine intramuscularly or intravenously, do not give more than 0.5 mg per minute. The dosage may be repeated at 5 to 10 minute intervals until a therapeutic effect is obtained or a maximum dose of 2 mg is attained.

Physostigmine may not be effective in reversing large overdoses and patients may need to be maintained with respiratory support.

If lumbar puncture is not contraindicated, consideration should be given to withdrawing 30 to 40 mL of CSF to reduce CSF baclofen concentration.

11 DESCRIPTION

GABLOFEN (baclofen injection) is a muscle relaxant and antispastic. Baclofen's pharmacological class is a gamma-aminobutyric acid (GABA) ergic agonist. Baclofen's chemical name is 4-amino-3-(4-chlorophenyl) butanoic acid, and its structural formula is:

Baclofen

C10H12ClNO2

Baclofen is a white to off-white powder, with a molecular weight of 213.66. It is slightly soluble in water, very slightly soluble in methanol and ethanol, practically insoluble in acetone and ether, soluble in 0.1N hydrochloric acid, 0.1N sodium hydroxide, and insoluble in chloroform.

GABLOFEN is a sterile, pyrogen-free, isotonic solution free of antioxidants, preservatives or other potentially neurotoxic additives indicated only for intrathecal administration. The drug is stable in solution at 37°C and compatible with CSF. Each mL of GABLOFEN contains baclofen USP 50 mcg, 500 mcg, 1,000 mcg or 2,000 mcg and sodium chloride 9 mg in Water for Injection; pH range is 5.5 to 7.5.

12 CLINICAL PHARMACOLOGY

12.1 Mechanism of Action

The precise mechanism of action of baclofen as a muscle relaxant and antispasticity agent is not fully understood. Baclofen inhibits both monosynaptic and polysynaptic reflexes at the spinal level, possibly by decreasing excitatory neurotransmitter release from primary afferent terminals, although actions at supraspinal sites may also occur and contribute to its clinical effect. Baclofen is a structural analog of the inhibitory neurotransmitter gamma-aminobutyric acid (GABA), and may exert its effects by stimulation of the GABAB receptor subtype.
Baclofen when introduced directly into the intrathecal space permits effective CSF concentrations to be achieved with resultant plasma concentrations 100 times less than those occurring with oral administration. In people, as well as in animals, baclofen has been shown to have general CNS depressant properties as indicated by the production of sedation with tolerance, somnolence, ataxia, and respiratory and cardiovascular depression.

12.2 Pharmacodynamics

Intrathecal Bolus

Adult Patients
The onset of action is generally one-half hour to one hour after an intrathecal bolus. Peak spasmolytic effect is seen at approximately four hours after dosing and effects may last four to eight hours. Onset, peak response, and duration of action may vary with individual patients depending on the dose and severity of symptoms.
Pediatric Patients
The onset, peak response and duration of action are similar to those seen in adult patients.
Continuous Infusion
Adult Patients
Intrathecal baclofen's antispastic action is first seen at 6 to 8 hours after initiation of continuous infusion. Maximum activity is observed in 24 to 48 hours.
Pediatric Patients
No additional information on continuous infusions is available for pediatric patients.

12.3 Pharmacokinetics

The pharmacokinetics of cerebrospinal fluid (CSF) clearance of intrathecal baclofen calculated from intrathecal bolus or continuous infusion studies approximates CSF turnover, suggesting elimination is by bulk-flow removal of CSF.

Intrathecal Bolus
After a bolus lumbar injection of 50 mcg or 100 mcg intrathecal baclofen in seven patients, the average CSF elimination half-life was 1.51 hours over the first four hours and the average CSF clearance was approximately 30 mL/hour.
Continuous Infusion
The mean CSF clearance for intrathecal baclofen was approximately 30 mL/hour in a study involving ten patients on continuous intrathecal infusion. Concurrent plasma concentrations of baclofen during intrathecal administration are expected to be low (0 to 5 ng/mL). Limited pharmacokinetic data suggest that a lumbar-cisternal concentration gradient of about 4:1 is established along the neuroaxis during baclofen infusion. This is based upon simultaneous CSF sampling via cisternal and lumbar tap in 5 patients receiving continuous baclofen infusion at the lumbar level at doses associated with therapeutic efficacy; the interpatient variability was great. The gradient was not altered by position. Six pediatric patients (age 8 to 18 years) receiving continuous intrathecal baclofen infusion at doses of 77 to 400 mcg/day had plasma baclofen levels near or below 10 ng/mL.

13 NONCLINICAL TOXICOLOGY

13.1 Carcinogenesis, Mutagenesis, Impairment of Fertility

Carcinogenesis

No increase in tumors was seen in rats receiving baclofen orally for two years.

Mutagenesis

Mutagenicity assays with baclofen have not been performed.

Impairment of Fertility

Studies to assess the potential for adverse effects of baclofen on fertility have not been conducted.

14 CLINICAL STUDIES

Spasticity of Spinal Cord Origin

Evidence supporting the efficacy of intrathecal baclofen was obtained in randomized, controlled investigations that compared the effects of either a single intrathecal dose or a three day intrathecal infusion of intrathecal baclofen to placebo in patients with severe spasticity and spasms due to either spinal cord trauma or multiple sclerosis. Intrathecal baclofen was superior to placebo on both principal outcome measures employed: change from baseline in the Ashworth rating of spasticity and the frequency of spasms.
Spasticity of Cerebral Origin
The efficacy of intrathecal baclofen was investigated in three controlled clinical trials; two enrolled patients with cerebral palsy and one enrolled patients with spasticity due to previous brain injury. The first study, a randomized controlled cross-over trial of 51 patients with cerebral palsy, provided strong, statistically significant results; intrathecal baclofen was superior to placebo in reducing spasticity as measured by the Ashworth Scale. A second cross-over study was conducted in 11 patients with spasticity arising from brain injury. Despite the small sample size, the study yielded a nearly significant test statistic (p=0.066) and provided directionally favorable results. The last study, however, did not provide data that could be reliably analyzed.

16 HOW SUPPLIED/STORAGE AND HANDLING

GABLOFEN (baclofen injection) is a clear, colorless, sterile, pyrogenfree, isotonic solution supplied as follows:

Package Type | Strength (Concentration) | NDC
Single-dose syringe | 50 mcg per mL | 66794-151-01
Single-dose syringe | 10,000 mcg per 20 mL (500 mcg/mL) | 66794-155-01
Single-dose syringe | 20,000 mcg per 20 mL (1,000 mcg/mL) | 66794-156-01
Single-dose syringe | 40,000 mcg per 20 mL (2,000 mcg/mL) | 66794-157-01
Single-dose vial | 10,000 mcg per 20 mL (500 mcg/mL) | 66794-155-02
Single-dose vial | 20,000 mcg per 20 mL (1,000 mcg/mL) | 66794-156-02
Single-dose vial | 40,000 mcg per 20 mL (2,000 mcg/mL) | 66794-157-02

Pump Refill Kits are supplied as requested by healthcare professionals in the following models:

- The Pump Refill Kit Model 9000 is supplied for use in combination with single-dose syringes of GABLOFEN (baclofen injection).
- The Pump Refill Kit Model 8500 is supplied for use in combination with single-dose vials of GABLOFEN (baclofen injection).

16.2 Storage and Handling
Store between 20°C and 25°C (68°F and 77°F). Do not store above 30°C (86°F).
Does not require refrigeration. Do not freeze. Do not heat sterilize.
Discard any unused portion.

17 PATIENT COUNSELING INFORMATION

Risks Related to Sudden Withdrawal of GABLOFEN

Advise patients and caregivers that sudden withdrawal of GABLOFEN, regardless of the cause, can result in serious complications that include high fever, confusion, muscle stiffness, multiple organ-system failure, and death. Inform patients that early symptoms of GABLOFEN withdrawal may include increased spasticity, itching, and tingling of extremities. If GABLOFEN withdrawal or a pump malfunction is suspected, patients should be brought immediately to a hospital for assessment and treatment.

Inform patients and caregivers that sudden withdrawal occurs most frequently due to a delivery problem with the catheter or the pump, or failure to refill the pump on schedule. Advise patients and their caregivers to pay careful attention to infusion system alarms. Instruct patients and caregivers that if they miss their scheduled pump refill, they should immediately contact their physician to reschedule the refill before the pump runs out of drug.

GABLOFEN Overdose

Inform patients and their caregivers that GABLOFEN overdose may occur suddenly or insidiously, and that symptoms may include confusion, drowsiness, lightheadedness, dizziness, slow or shallow breathing, seizures, loss of muscle tone, loss of consciousness, and coma. If an overdose appears likely, patients should be brought immediately to a hospital for assessment and possible emptying of the pump.

Operation of Automobiles and Other Dangerous Machinery

Advise patients that GABLOFEN may cause drowsiness, and that they should exercise caution regarding the operation of automobiles or other dangerous machinery, or activities made hazardous by decreased alertness.

Increased Risk of Drowsiness with Alcohol and Other CNS Depressants

Inform patients and their caregivers that the drowsiness associated with GABLOFEN use can be worsened by alcohol and other CNS depressants. Advise patients to read all medicine labels carefully, and to tell their physician about all prescription and nonprescription drugs they may use.

Manufactured for:

Piramal Critical Care, Inc.

3950 Schelden Circle

Bethlehem, PA 18017, USA

Phone: 888 822 8431

Issued 12/2024

PACKAGE LABEL

Gablofen®

(Baclofen injection)

50 mcg/mL

For intrathecal use only

NDC 66794-151-01

Contains one x 1 mL

Gablofen® (baclofen injection)

10,000 mcg/20 mL

(500 mcg/mL)

Sterile solution for intrathecal use only

NDC 66794-155-01

Contains one x 20 mL syringe

Gablofen® (baclofen injection)

10,000 mcg/20 mL

(500 mcg/mL)

Sterile solution for intrathecal use only

NDC 66794-155-02

Gablofen®

(baclofen injection)

20,000 mcg/20 mL

(1,000 mcg/mL)

Sterile solution for intrathecal use only

NDC 66794-156-01

Contains one x 20 mL syringe

Gablofen®

(baclofen injection)

20,000 mcg/20 mL

(1,000 mcg/mL)

Sterile solution for intrathecal use only
NDC 66794-156-02

Gablofen® (baclofen injection)

40,000 mcg/20 mL

(2,000 mcg/mL)

Sterile solution for intrathecal use only

NDC 66794-157-01

Contains one x 20 mL syringe

Gablofen® (baclofen injection)

40,000 mcg/20 mL

(2,000 mcg/mL)

Sterile solution for intrathecal use only

NDC 66794-157-02